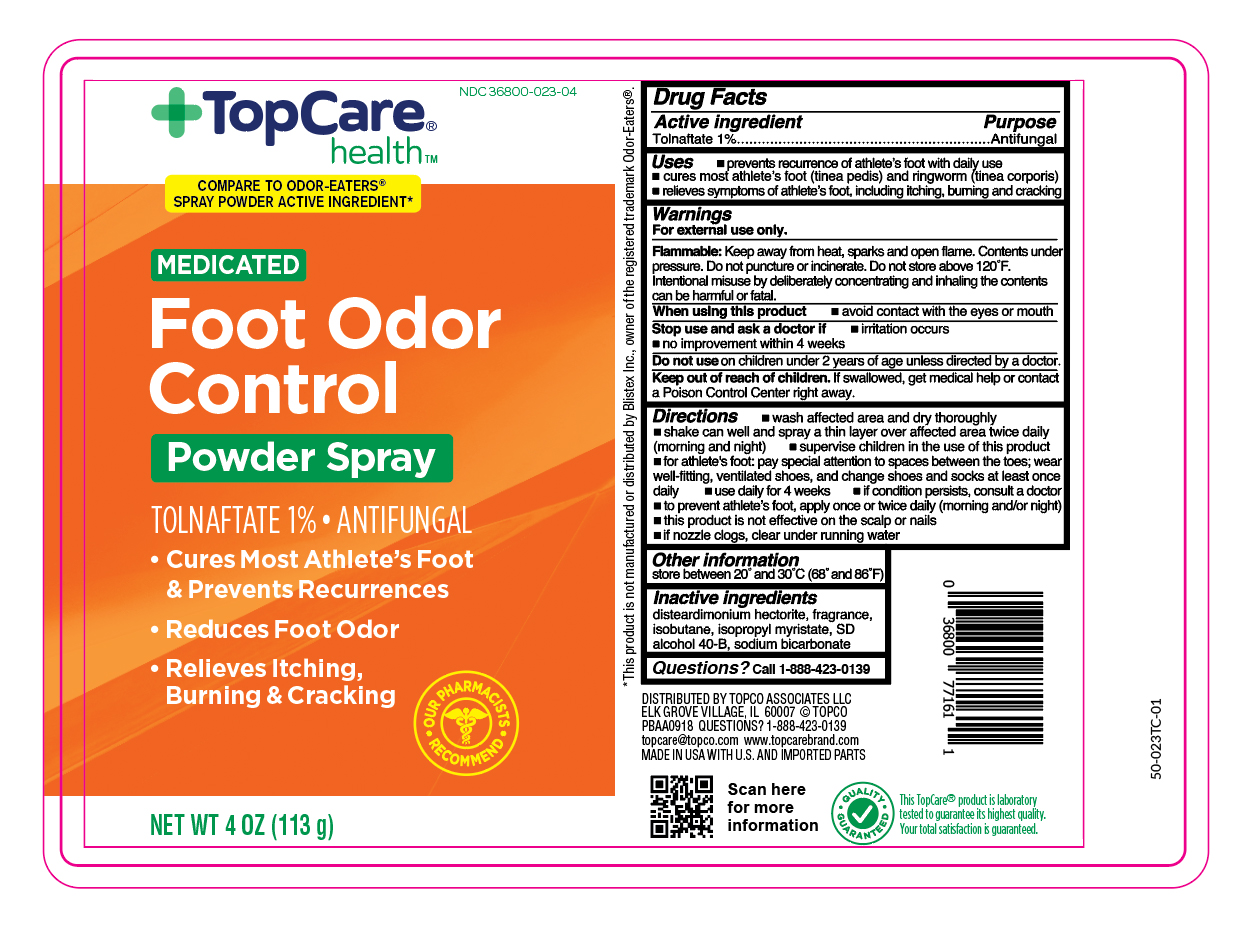 DRUG LABEL: Tolnaftate
NDC: 36800-023 | Form: AEROSOL, SPRAY
Manufacturer: Topco Associates LLC
Category: otc | Type: HUMAN OTC DRUG LABEL
Date: 20251106

ACTIVE INGREDIENTS: TOLNAFTATE 1.13 g/113 g
INACTIVE INGREDIENTS: DISTEARDIMONIUM HECTORITE; ISOBUTANE; ISOPROPYL MYRISTATE; ALCOHOL; SODIUM BICARBONATE

TopCare Foot Odor Control Spray

Active ingredient

Tolnaftate 1%

Purpose

Antifungal

Uses

- prevents recurrence of athlete's foot (tinea pedis) with daily use
- cures mose athlete's foot (tinea pedis) and ringworm (tinea corporis)
- relieves sypmtoms of athlete's foot, including itching, burning and cracking

Warnings

For external use only.

Flammable:

Keep away from heat, sparks and open flame. Contents under pressure. Do not puncture or incinerate. Do not store at temperature above 120ºF. Intentional misuse by deliberately concentrating and inhaling contents cans be harmful or fatal.

When using this product

- avoid contact with the eyes or mouth

Stop use and ask a doctor if

- irritation occurs
- no improvement within 4 weeks

Do not use

on children under 2 years of age unless directed by a doctor

Keep out of reach of children.

If swallowed, get medical help or contact a Poison Control Center right away.

Directions

- wash affected area and dry thoroughly
- shake can well and spray a thin layer over affected area twice daily (morning and night)
- supervise children in the use of this product
- for athlete's foot: pay special attention to spaces between the toes, wear well-fitting, ventilated shoes and change shoes and socks at least once daily
- use daily for 4 weeks
- if conditions persist, consult a doctor
- to prevent athlete's foot, apply once or twice daily (morning and/or night)
- in case of clogging, clear nozzle under running water

Other information

store between 20º and 30ºC (68ºF and 86º)

Inactive ingredients

disteardimonium hectorite, fragrance, isobutane, isopropyl myristate, SD alcohol 40-B, sodium bicarbonate

Questions?

call 1-866-964-0939

Principal Display Panel

TopCare

MEDICATED

Foot Odor

Control

Powder Spray

TOLNAFTATE % • ANTIFUNGAL

- Cures Most Athlete's Foot & Prevents Recurrences

- Reduces Foot Odor
- Relieves Itching, Burning & Cracking

NET WT 4 OZ (113g)